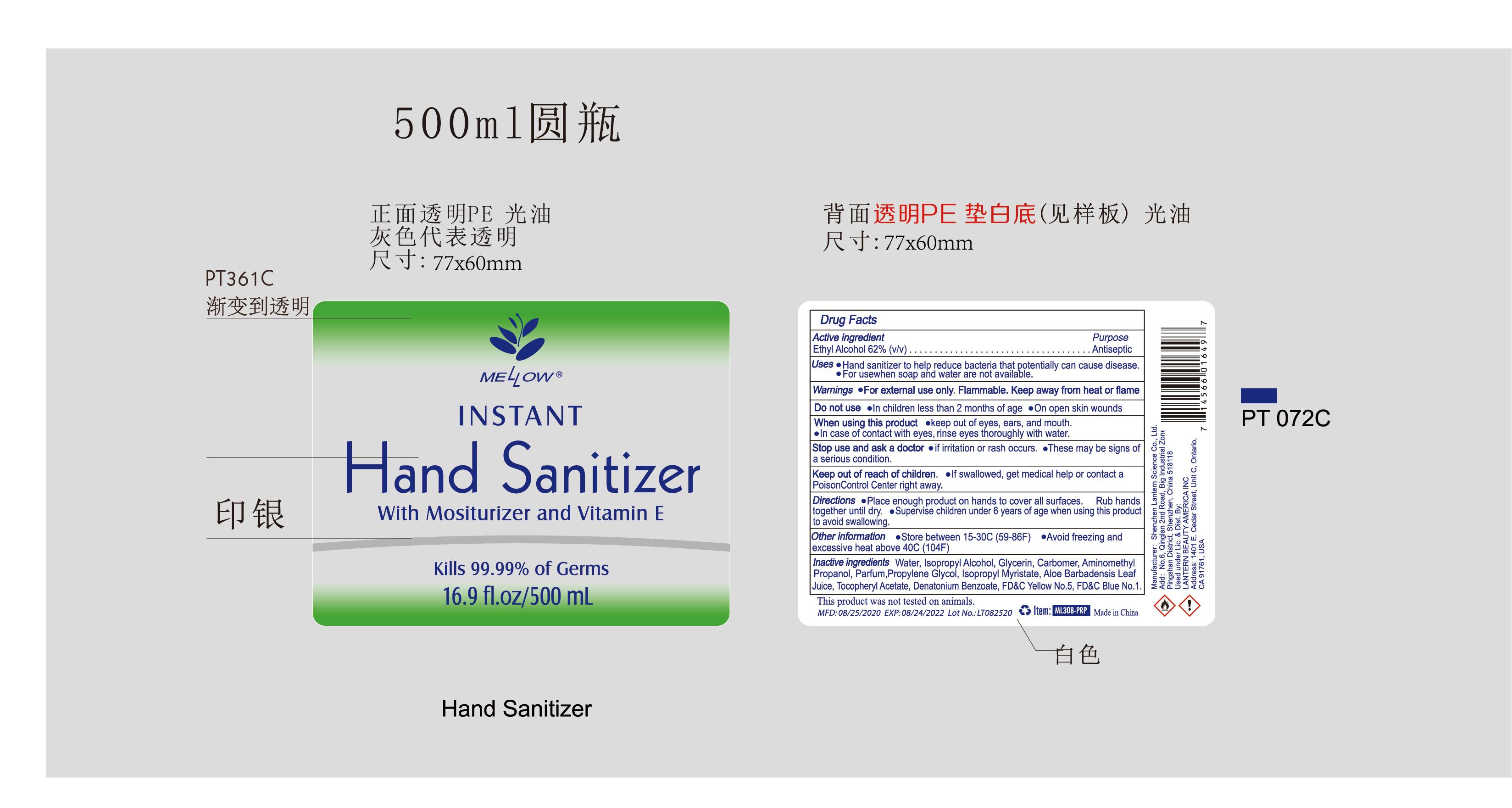 DRUG LABEL: Mellow hand sanitizer 500ml ML308-PRP
NDC: 54860-331 | Form: LIQUID
Manufacturer: Shenzhen Lantern Scicence Co.,Ltd.
Category: otc | Type: HUMAN OTC DRUG LABEL
Date: 20200910

ACTIVE INGREDIENTS: ALCOHOL 62 mL/100 mL
INACTIVE INGREDIENTS: PIGMENT BLUE 1 0.000024 mL/100 mL; PROPYLENE GLYCOL 0.1 mL/100 mL; ALOE VERA LEAF 0.1 mL/100 mL; ISOPROPYL MYRISTATE 0.001 mL/100 mL; ISOPROPYL ALCOHOL 0.5 mL/100 mL; .ALPHA.-TOCOPHEROL ACETATE 0.001 mL/100 mL; ALOE 0.1 mL/100 mL; AMINOMETHYLPROPANOL 0.12 mL/100 mL; WATER 36.376416 mL/100 mL; GLYCERIN 0.5 mL/100 mL; BASIC YELLOW 5 0.00006 mL/100 mL; CARBOMER 940 0.3 mL/100 mL

Mellow hand sanitizer 500ml ML308-PRP

Active Ingredient

Active Ingredient Purpose

Ethyl Alcohol 62%（V/V） Antiseptic

Use

Hand sanitizer to help reduce bacteria that potentially can cause disease.

For use when soap and water are not available.

Do not use

In children less than 2 months of age.

On open skin wounds.

DOSAGE AND ADMINISTRATION

Recommended for repeated use.

use anywhere without water.

Warning

For extenal use only:hands.

Flammable,Keep away from fire or flame.

WARNINGS AND PRECAUTIONS

For external use only.

Flammable, keep away from heat and flame.

STOP USE

Discontinue if skin becomes irritated and ask a doctor .

Keep out of reach of children. In case of accidental ingestion, seek professional assistance or contact a poson control center immediately.

Do not use

In children less than 2 months of age.

On open skin wounds

When using this product

Keep out of eyes,ears,and mouth.

In case of contact with eyes,rinse eyes thoroughly with water.

Stop use and ask a doctor

if irritation or rash occurs,these may be signs of a serious condition.

Keep out of reach of children

If swallowed,get medical help or contact a Poison Control Center right away.

Inactive ingredients

Alcohol，water，Isopropyl Alcohol，Glycerin，Carbomer，Aminomethyl Propanol，Parfum，Propylene Glycol，ISOPROPYL MYRISTATE，ALOE BARBADENSIS LEAF JUICE，Tocopheryl Acetate，YELLOW No.5，FD&C BLUE No. 1.

Directions

Place enough product on hands to cover all surfaces.Rub hands together until dry.Supervise children under 6 years of age when using this product to avoid swallowing.

When using this product

keep out of eyes. In case of contact with eyes, flush thoroughly with water.

Do not inhale or ingest.

Avoid contact with broken skin.

Other information

Do not store above 105F.

May discolor some fabrics.

Harmful to wood finishes and plastics.

Other information

Store between 15-30C

Avoid freezing and excessive heat above 40C